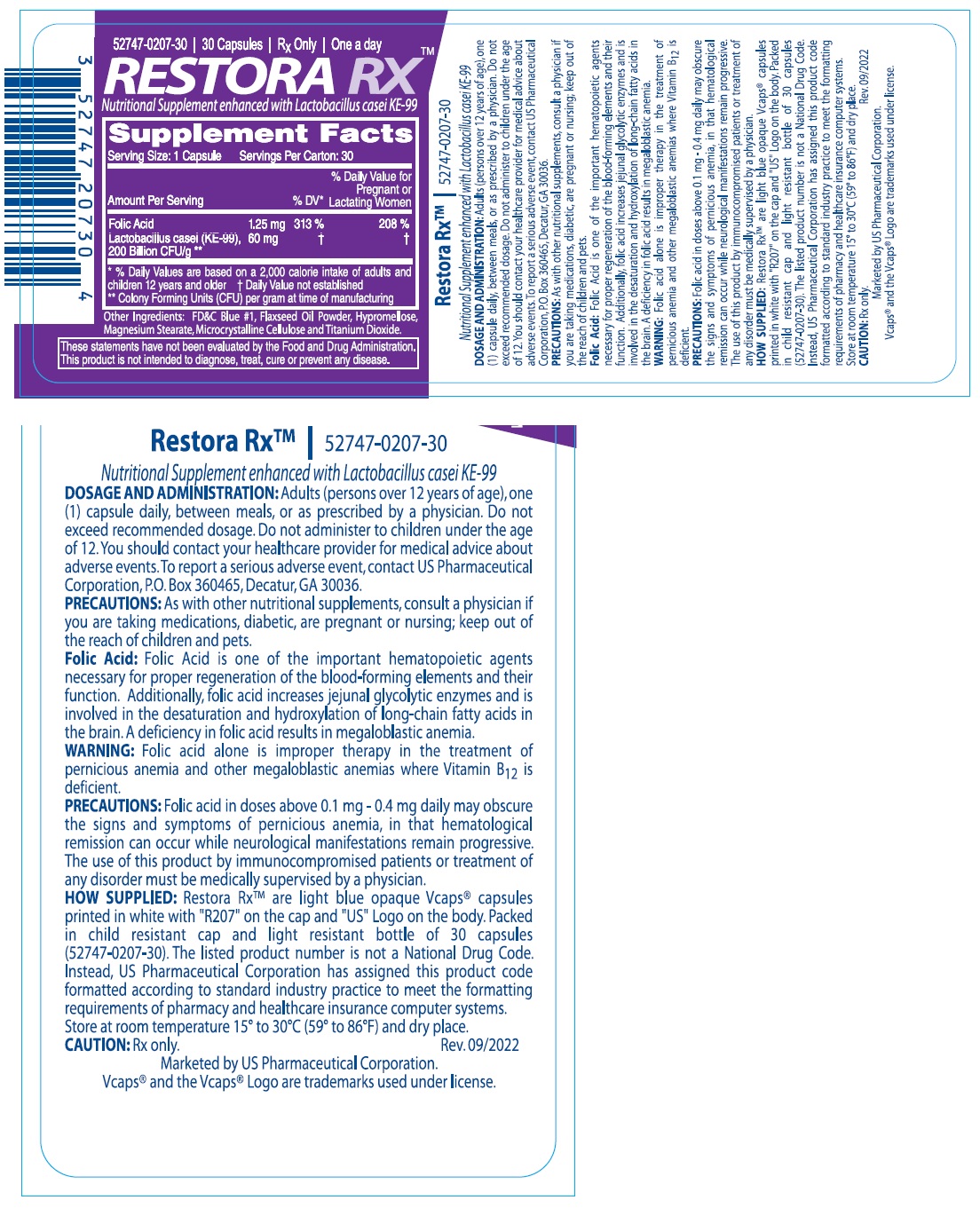 DRUG LABEL: RESTORA RX
NDC: 52747-207 | Form: CAPSULE
Manufacturer: U.S. Pharmaceutical Corporation
Category: other | Type: DIETARY SUPPLEMENT
Date: 20230612

ACTIVE INGREDIENTS: FOLIC ACID 1.25 mg/1 1; LACTICASEIBACILLUS CASEI 60 mg/1 1
INACTIVE INGREDIENTS: FD&C BLUE NO. 1; LINSEED OIL; HYPROMELLOSE, UNSPECIFIED; MAGNESIUM STEARATE; MICROCRYSTALLINE CELLULOSE; TITANIUM DIOXIDE

RESTORA RX™

STATEMENT OF IDENTITY

Supplement Facts
Serving Size: 1 Capsule Servings Per Carton: 30

Amount Per Serving

% DV*

% Daily Value for
Pregnant or

Lactating Women

Folic Acid
Lactobacillus casei (KE-99),
200 Billion CFU/g **

1.25 mg

60 mg

313%

†

208%

†

* % Daily Values are based on a 2,000 calorie intake of adults and children 12 years and older. † Daily Value not established
**Colony Forming Units (CFU) per gram at time of manufacturing

Other Ingredients: FD&C Blue #1, Flaxseed Oil Powder, Hypromellose, Magnesium Stearate, Microcrystalline Cellulose and Titanium Dioxide.

These statements have not been evaluated by the Food and Drug Administration. This product is not intended to diagnose, treat, cure or prevent any disease.

DOSAGE AND ADMINISTRATION: Adults (persons over 12 years of age), one (1) capsule daily, between meals, or as prescribed by a physician. Do not exceed recommended dosage. Do not administer to children under the age of 12. You should contact your healthcare provider for medical advice about adverse events. To report a serious adverse event, contact US Pharmaceutical Corporation, P.O. Box 360465, Decatur, GA 30036.

PRECAUTIONS

PRECAUTIONS: As with other nutritional supplements, consult a physician if you are taking medications, diabetic, are pregnant or nursing; keep out of the reach of children and pets.

Folic Acid: Folic Acid is one of the important hematopoietic agents necessary for proper regeneration of the blood-forming elements and their function. Additionally, folic acid increases jejunal glycolytic enzymes and is involved in the desaturation and hydroxylation of long-chain fatty acids in the brain. A deficiency in folic acid results in megaloblastic anemia.

WARNINGS

WARNING: Folic acid alone is improper therapy in the treatment of pernicious anemia and other megaloblastic anemias where Vitamin B12 is deficient.

PRECAUTIONS: Folic acid in doses above 0.1 mg - 0.4 mg daily may obscure the signs and symptoms of pernicious anemia, in that hematological remission can occur while neurological manifestations remain progressive. The use of this product by immunocompromised patients or treatment of any disorder must be medically supervised by a physician.

HOW SUPPLIED: Restora RxTM are light blue opaque Vcaps® capsules printed in white with “R207” on the cap and “US” Logo on the body. Packed in child resistant cap and light resistant bottle of 30 capsules (52747-0207-30). The listed product number is not a National Drug Code. Instead, US Pharmaceutical Corporation has assigned this product code formatted according to standard industry practice to meet the formatting requirements of pharmacy and healthcare insurance computer systems.

SAFE HANDLING WARNING

Store at room temperature 15° to 30°C (59° to 86°F) and dry place.

CAUTION: Rx only. Rev.09/2022

Marketed by US Pharmaceutical Corporation.
Vcaps® and the Vcaps® Logo are trademarks used under license.

HEALTH CLAIM

Nutritional Supplement enhanced with Lactobacillus casei KE-99